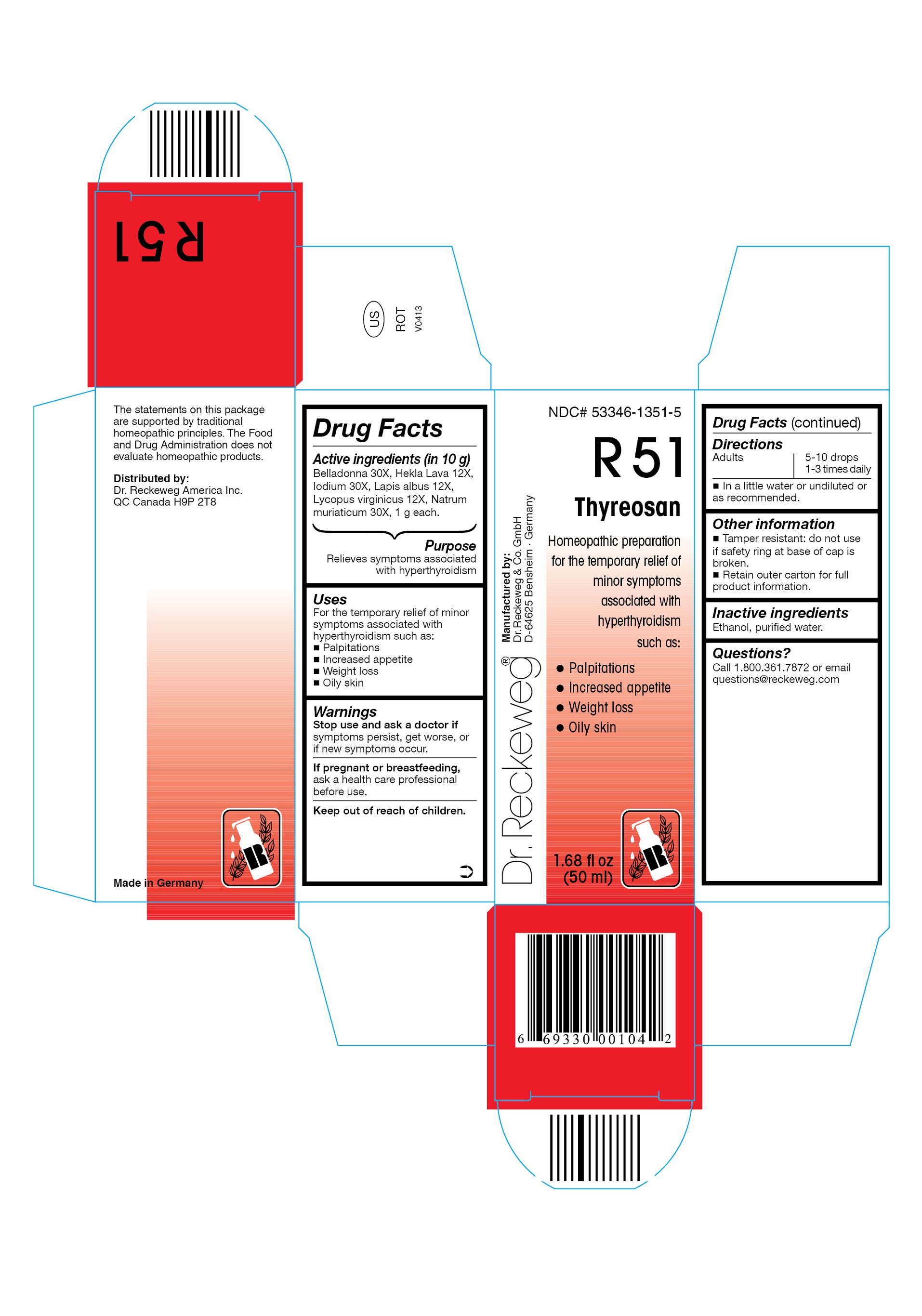 DRUG LABEL: DR. RECKEWEG R51 Thyreosan
NDC: 53346-1351 | Form: LIQUID
Manufacturer: PHARMAZEUTISCHE FABRIK DR. RECKEWEG & CO
Category: homeopathic | Type: HUMAN OTC DRUG LABEL
Date: 20130405

ACTIVE INGREDIENTS: ATROPA BELLADONNA 30 [hp_X]/50 mL; HEKLA LAVA 12 [hp_X]/50 mL; IODINE 30 [hp_X]/50 mL; CALCIUM HEXAFLUOROSILICATE 12 [hp_X]/50 mL; LYCOPUS VIRGINICUS 12 [hp_X]/50 mL; SODIUM CHLORIDE 30 [hp_X]/50 mL
INACTIVE INGREDIENTS: ALCOHOL; WATER

DR. RECKEWEG R51 Thyreosan

Active ingredients

Belladonna 30X, Hekla Lava 12X, Iodium 30X, Lapis albus 12X, Lycopus virginicus 12X, Natrum muriaticum 30X, 1 g each in 10 g.

Purpose

Relieves symptoms associated with hyperthyroidism

Uses

For the temporary relief of minor symptoms associated with hyperthyroidism such as:

- Palpitations
- Increased appetite
- Weight loss
- Oily skin

Warnings

Stop use and ask a doctor if symptoms persist, get worse, or if new symptoms occur.

PREGNANCY OR BREAST FEEDING

If pregnant or breastfeeding, ask a health care professional before use.

Keep out of reach of children.

Directions
Adults 5-10 drops 1-3 times daily in a little water or undiluted or as recommended.

Other information

- Tamper resistant: do not use if safety ring at base of cap is broken.
- Retain outer carton for full product information.

Inactive ingredients

Ethanol, purified water.

Questions?

Call 1-800-361-7872 or email questions@reckeweg.com

PACKAGE LABEL

NDC# 53346-1351-5

Dr. Reckeweg R51 Thyreosan

Homeopathic preparation for the temporary relief of minor symptoms associated with hyperthyroidism such as:

- Palpitations
- Increased appetite
- Weight loss
- Oily skin

Manufactured by:

Dr. Reckeweg Co. GmbH

D-64625 Bensheim

Germany

1.68 fl oz
(50 ml)